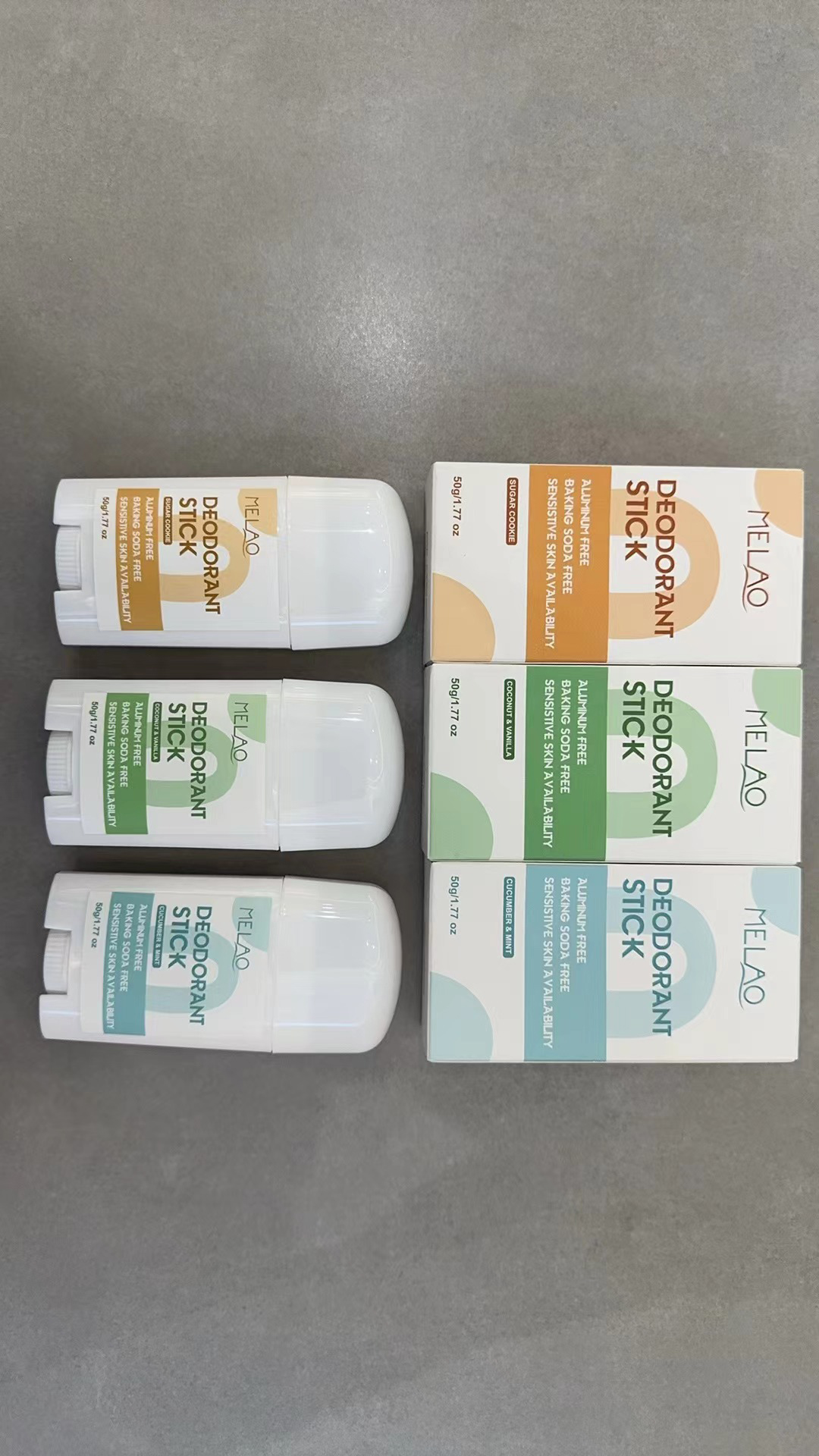 DRUG LABEL: MELAO deodorant stick
NDC: 83566-599 | Form: STICK
Manufacturer: Guangzhou Yilong Cosmetics Co,Ltd.
Category: otc | Type: HUMAN OTC DRUG LABEL
Date: 20240731

ACTIVE INGREDIENTS: ETHYLHEXYL PALMITATE 10 g/100 g
INACTIVE INGREDIENTS: PEG-8 BEESWAX; GLYCERYL STEARATE CITRATE; MINERAL OIL; TOCOPHEROL; DIMETHICONE CROSSPOLYMER (450000 MPA.S AT 12% IN CYCLOPENTASILOXANE); COCOS NUCIFERA WHOLE; 4-METHYL-1,4-PENTANEDIYL DIMETHACRYLATE; PARAFFIN; DRYOBALANOPS AROMATICA RESIN; .BETA.-BISABOLOL; MAGNESIUM HYDROXIDE; PROPYLPARABEN

Active ingredients

Ethylhexyl Palmitate 10%

Purpose

Antiperspirant fragrance

Uses

Spin the stick out. Using the stick apply to armpitor to bodyskin.

warnings

For external use only.

Stop use and ask a doctor if

rash occurs.

Do not use

on damaged or broken skin.

When using this product

keep out of eyes. Rinse withwater to remove.

Keep out of reach of children.

If swallowed, get medical help or contact a Poison Control Center right away.

dosage

Squeeze out an appropriate amount of deodorant stick and spread evenly on skin,

inactive ingredients

Cyclopentasiloxane 35%

Magnesium Hydroxide 13%

Beeswax 12%

Ozokerite 8%

Ozokerite 6%

Cocos Nucifera (Coconut) Oil 5%

GlycerylStearate 5%

Aroma 3%

Tocophero 2%

Bisabolol 0.5%

BHT 0.3%

Propylparaben 0.2%